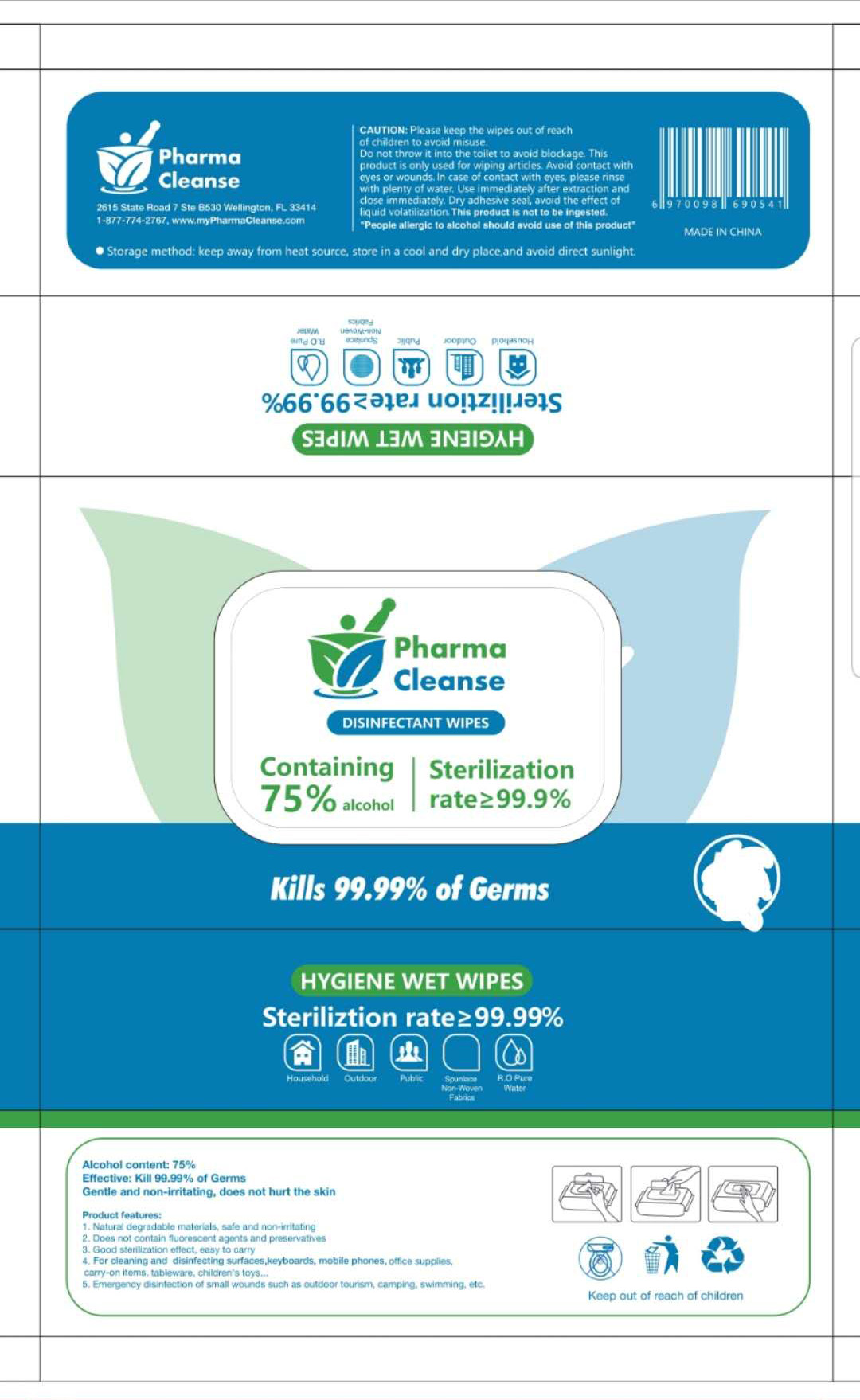 DRUG LABEL: Hand Sanitizer wipes
NDC: 78150-002 | Form: CLOTH
Manufacturer: Zhejiang Yiwu Caijie Daily Necessities Factory
Category: otc | Type: HUMAN OTC DRUG LABEL
Date: 20200628

ACTIVE INGREDIENTS: ALCOHOL 75 mL/100 g
INACTIVE INGREDIENTS: WATER

Hand sanitizer wipes

Active Ingredient(s)

Alcohol 75%. Purpose: Antiseptic

Purpose

Antiseptic, Hand Sanitizer wipes

Use

kills 99.99% of germs

Warnings

Please keep the wipes out of reach of children to avoid misue.

Do not throw it into the toilet to avoid blockage. This product is only used for wiping articles. Avoid contact with eyes or wounds. In case of contact with eyes, please rinse with plenty of water. Use immediately after extraction and close immediately. Dry adhesive seal, avoid the effect of liquid volatilization. This product is not to be ingested.

People allergic to alcohol should avoid use of this product

This product is not to be ingested.

People allergic to alcohol should avoid use of this product

WHEN USING

Avoid contact with eyes or wounds. In case of contact with eyes, please rinse with plenty of water.

KEEP OUT OF REACH OF CHILDREN

Please keep the wipes out of reach of children to avoid misue. This product is not to be ingested.

Directions

Use immediately after extraction and close immediately. Dry adhesive seal, avoid the effect of liquid volatilization.

Other information

Keep away from heat source, store in a cool and dry place. and avoid direct sunlight

Inactive ingredients

water

Package Label - Principal Display Panel

160 PCS 78150-002-01